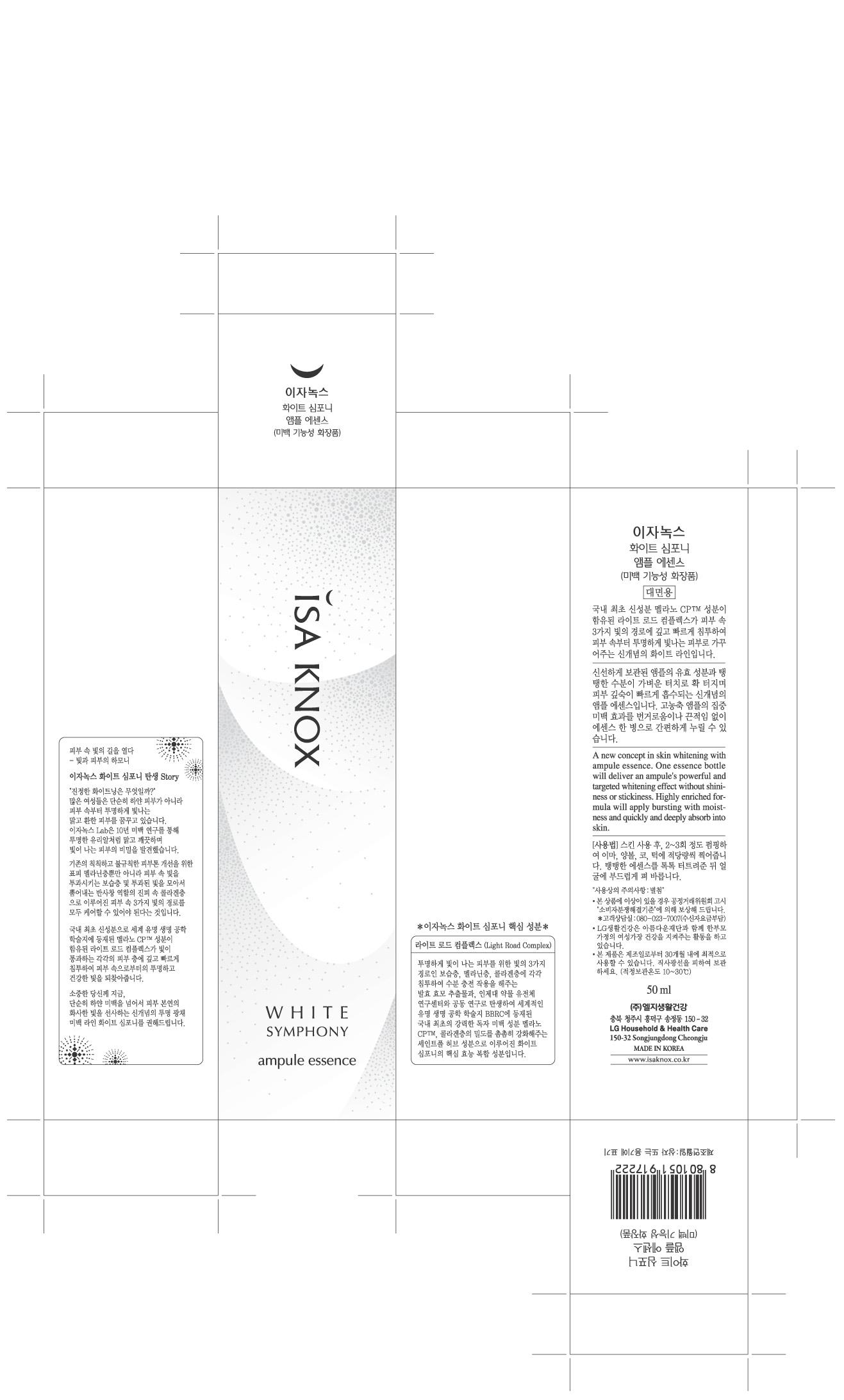 DRUG LABEL: ISA KNOX WHITE SYMPHONY AMPULE ESSENCE
NDC: 53208-414 | Form: CREAM
Manufacturer: LG Household and Healthcare, Inc.
Category: otc | Type: HUMAN OTC DRUG LABEL
Date: 20100524

ACTIVE INGREDIENTS: ATRACTYLODES JAPONICA ROOT 0.0525 mL/100 mL
INACTIVE INGREDIENTS: WATER; ALCOHOL; DIPROPYLENE GLYCOL; 2-ETHYLHEXANOIC ACID; CYCLOMETHICONE 5; GLYCERIN; BUTYLENE GLYCOL; CAPRIC ACID; DIMETHICONE; POLYSORBATE 60; GLYCERYL MONOSTEARATE; PANTHENOL; BETAINE; TROLAMINE; METHYLPARABEN; PROPYLPARABEN; EDETATE TRISODIUM

Drug Facts

ACTIVE INGREDIENT

ATRACTYLODES JAPONICA ROOT 0.525ml/100ml

WARNINGS AND PRECAUTIONS

For external use only.

Keep out of reach of children. Is swallowed, get medical help or contact a Poison Control Center right away.

WHEN USING

Keep out of eyes. Rinse with water to remove.

PACKAGE LABEL

ISAKNOX
WHITE SYMPHONY
AMPULE ESSENCE